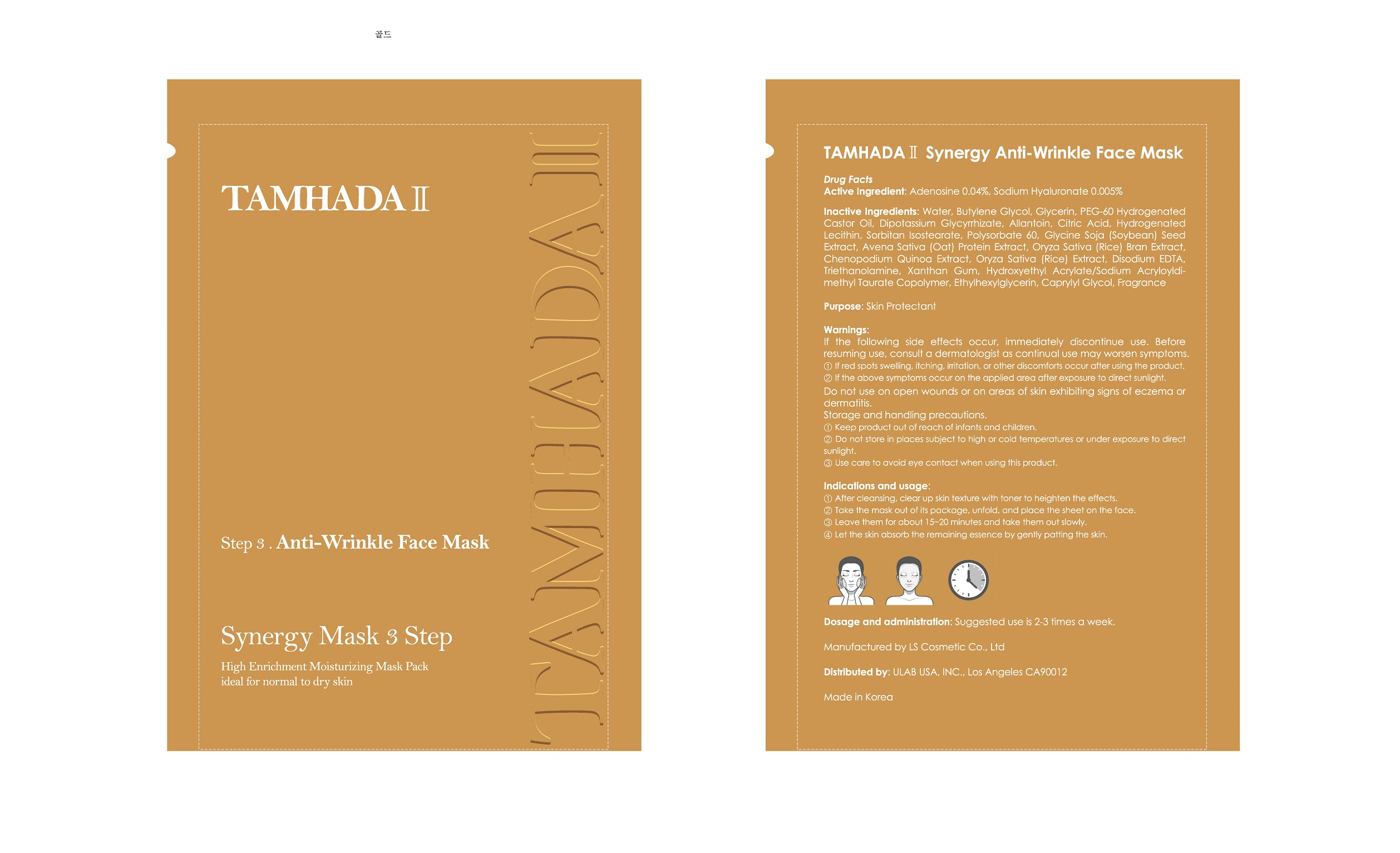 DRUG LABEL: TAMHADA II Synergy Anti-Wrinkle Face Mask
NDC: 72547-0004 | Form: LIQUID
Manufacturer: SE KWANG S.T CORPORATION
Category: otc | Type: HUMAN OTC DRUG LABEL
Date: 20180904

ACTIVE INGREDIENTS: GLYCERIN 4.4 g/100 mL
INACTIVE INGREDIENTS: WATER; ALLANTOIN

Drug Facts

ACTIVE INGREDIENT

Glycerin

INACTIVE INGREDIENT

Water
Butylene Glycol
PEG-60 Hydrogenated Castor Oil
Adenosine
Dipotassium Glycyrrhizate
Allantoin
Citric Acid
Hydrogenated Lecithin
Sodium Hyaluronate
Sorbitan Isostearate
Polysorbate 60
Glycine Soja (Soybean) Seed Extract
Avena Sativa (Oat) Protein Extract
Oryza Sativa (Rice) Bran Extract
Chenopodium Quinoa Extract
Oryza Sativa (Rice) Extract
Disodium EDTA
Triethanolamine
Xanthan Gum
Hydroxyethyl Acrylate/Sodium Acryloyldimethyl Taurate Copolymer
Ethylhexylglycerin
Caprylyl Glycol
Fragrance

PURPOSE

Skin protectant

keep out of reach of the children

INDICATIONS AND USAGE

1. After cleansing, clear up skin texture with toner to heighten the effects.
2. Take the mask out of its package, unfold, and place the sheet on the face
3. Leave them for about 15-20 minutes and take them out slowly.
4. Let the skin absorb the remaining essence by gently patting the skin.

DOSAGE AND ADMINISTRATION

for external use only

WARNINGS

1. If the following symptoms occur after product use, stop using the product immediately and consult a dermatologist (continuous use can exacerbate the symptoms).
1) Occurrence of red spots, swelling, itchiness, and other skin irritation
2) If the symptoms above occur after the application area is exposed to direct sunlight
2. Do not use on open wounds, eczema, and other skin irritations
3. Precaution for Storage and Handling
1) Close the lid after use
2) Keep out of reach of infants and children
3) Do not to store in a place with high/low temperature and exposed to direct sunlight